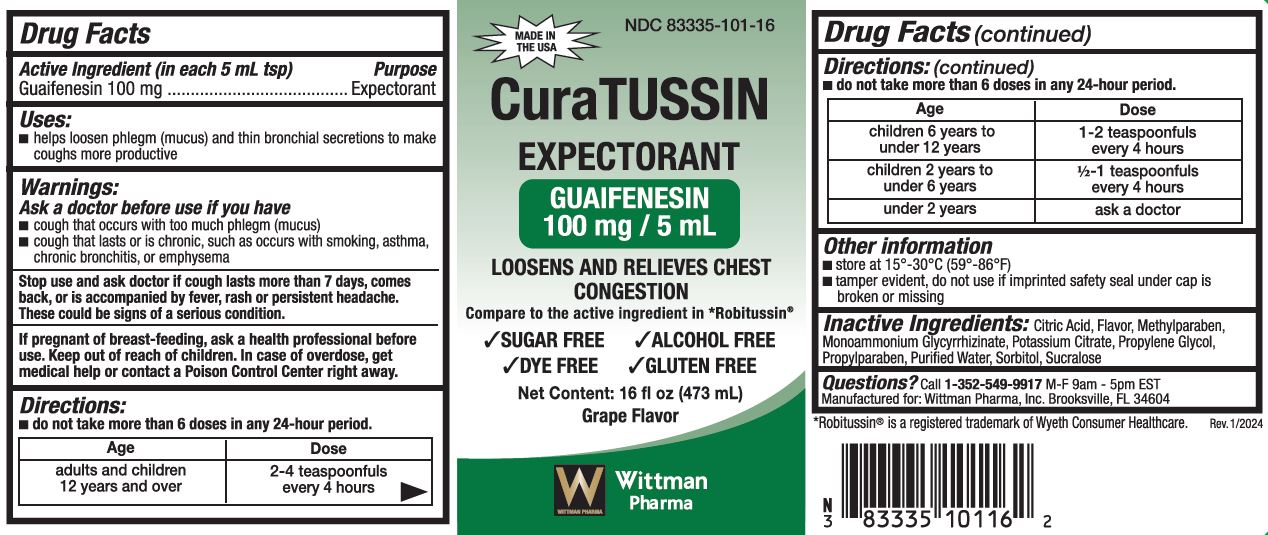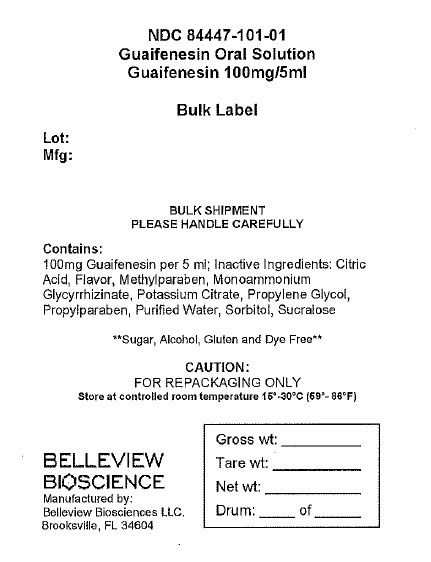 DRUG LABEL: Guaifenesin 100mg/5mL
NDC: 84447-101 | Form: SOLUTION
Manufacturer: Belleview Biosciences
Category: otc | Type: HUMAN OTC DRUG LABEL
Date: 20241120

ACTIVE INGREDIENTS: GUAIFENESIN 100 mg/5 mL
INACTIVE INGREDIENTS: PROPYLENE GLYCOL; SUCRALOSE; PROPYLPARABEN; POTASSIUM CITRATE; METHYLPARABEN; ANHYDROUS CITRIC ACID; AMMONIUM GLYCYRRHIZATE; SORBITOL; WATER

Guaifenesin Oral Solution 100mg/5mL

Dosage & Admin

Directions:

■ do not take more than 6 doses in any 24-hour period.

AGE | DOSE
Adults & Children 12 years and over | 2-4 teaspoonfuls every 4 hours
Children 6 years to under 12 years | 1-2 teaspoonfuls every 4 hours
Children 2 to under 6 years | 1/2 - 1 teaspoonfuls every 4 hours
Children Under 2 years | Ask a Doctor

Warnings

Ask a doctor before use if you have

■ cough that occurs with too much phlegm (mucus)

■ cough that lasts or is chronic, such as occurs with smoking, asthma,

Chronic bronchitis, or emphysema

Stop use and ask a doctor if cough lasts more than 7 days, comes

back, or is accompanied by fever, rash or persistent headache.

These could be signs of a serious condition.

If pregnant of breast-feeding, ask a health professional before

use. Keep out of reach of children. In case of overdose, get

medical help or contact a Poison Control Center right away.

INACTIVE INGREDIENT

Inactive Ingredients: Citric Acid, Flavor, Methylparaben, Monoammonium Glycyrrhizinate, Potassium Citrate, Propylene Glycol, Propylparaben, Purified Water, Sorbitol, Sucralose

Uses:

■ helps loosen phlegm (mucus) and thin bronchial secretions to make

coughs more productive

Keep out of reach of children. In case of overdose, get

medical help or contact a Poison Control Center right away.

Purpose: Expectorant

Active Ingredient (in each 5 mL tsp)

Guaifenesin 100 mg